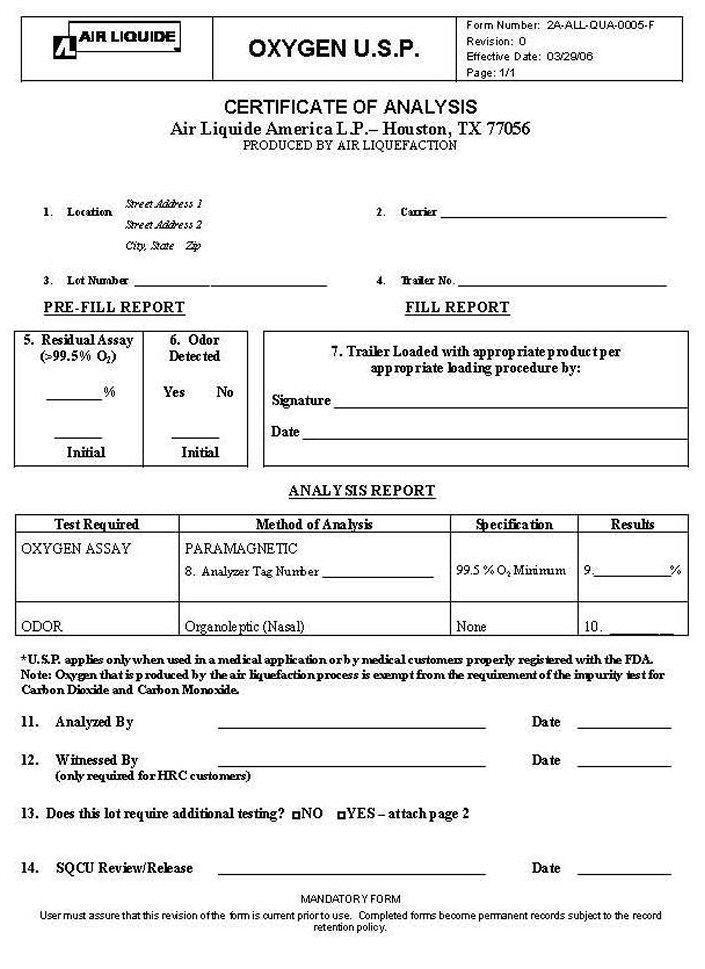 DRUG LABEL: OXYGEN
NDC: 10671-013 | Form: GAS
Manufacturer: Air Liquide America L.P.
Category: prescription | Type: HUMAN PRESCRIPTION DRUG LABEL
Date: 20150219

ACTIVE INGREDIENTS: OXYGEN 99 L/100 L

OXYGEN USP CERTIFICATE OF ANALYSIS